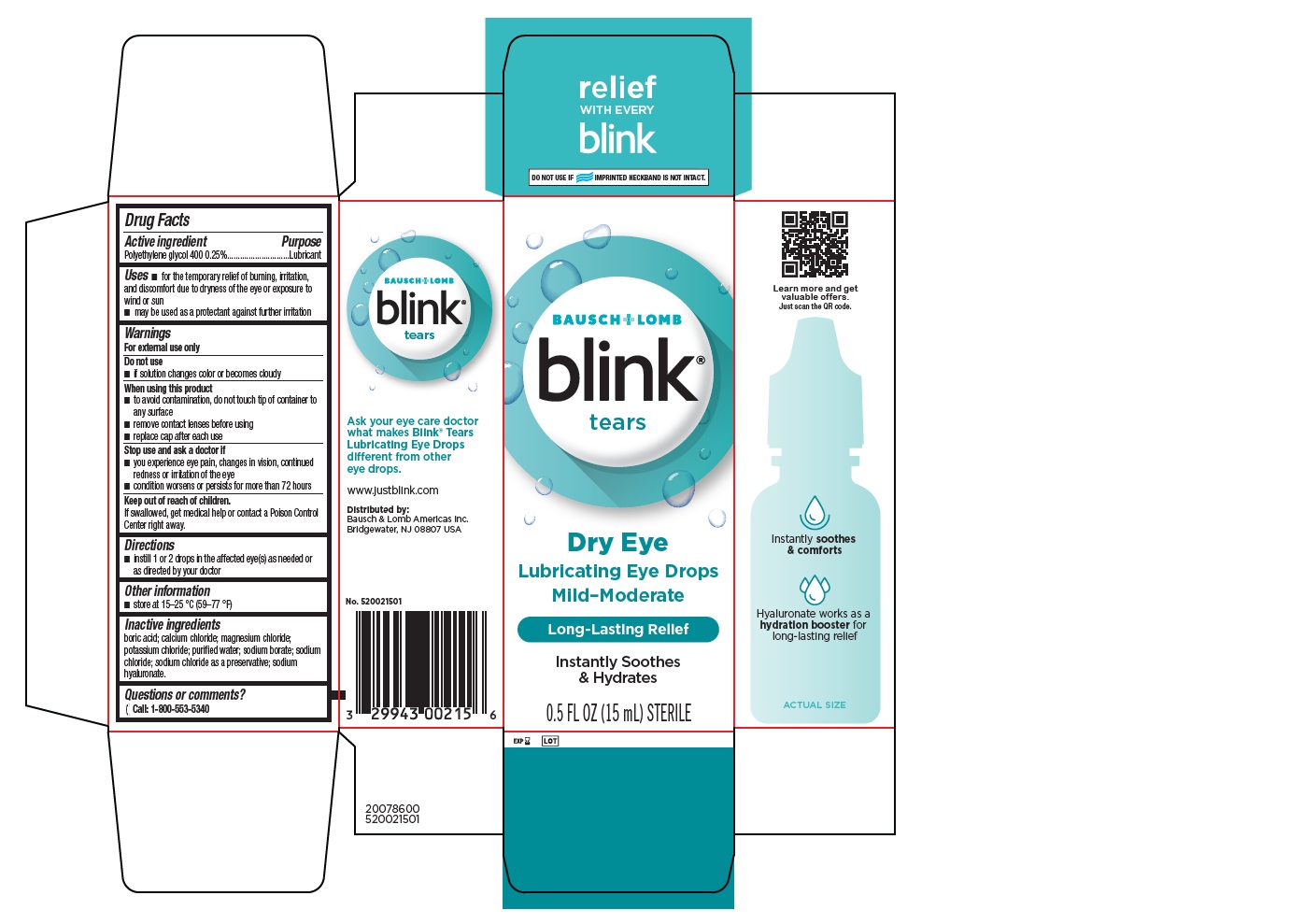 DRUG LABEL: blink tears
NDC: 29943-002 | Form: SOLUTION/ DROPS
Manufacturer: Bausch & Lomb Incorporated
Category: otc | Type: HUMAN OTC DRUG LABEL
Date: 20250820

ACTIVE INGREDIENTS: POLYETHYLENE GLYCOL 400 2.5 mg/1 mL
INACTIVE INGREDIENTS: BORIC ACID; CALCIUM CHLORIDE; MAGNESIUM CHLORIDE; POTASSIUM CHLORIDE; WATER; SODIUM BORATE; SODIUM CHLORIDE; SODIUM CHLORITE; HYALURONATE SODIUM

Drug Facts

Active ingredient

Polyethylene glycol 400 0.25%

Purpose

Lubricant

Uses

- for the temporary relief of burning, irritation and discomfort due to dryness of the eye or exposure to wind or sun
- may be used as a protectant against further irritation

Warnings

For external use only

Do not use

- if solution changes color or becomes cloudy

When using this product

- to avoid contamination, do not touch tip of container to any surface
- remove contact lenses before using
- replace cap after each use

Stop use and ask a doctor if

- you experience eye pain, changes in vision, continued redness or irritation of the eye
- condition worsens or persists for more than 72 hours

Keep out of reach of children.

If swallowed, get medical help or contact a Poison Control Center right away.

Directions

- instill 1 or 2 drops in the affected eye(s) as needed or as directed by your doctor

Other Information

- store at 15-25 °C (59-77 °F)

Inactive ingredients

boric acid; calcium chloride; magnesium chloride; potassium chloride; purified water; sodium borate; sodium chloride; sodium chloride as a preservative; sodium hyaluronate.

Questions or comments?

[phone icon] call: 1-800-553-5340

Principal Display Panel - 15 mL Bottle Carton

BAUSCH + LOMB

blink®
tears

Dry Eye
Lubricating Eye Drops
Mild-Moderate

Long-Lasting Relief

Instantly Soothes
& Hydrates

0.5 FL OZ (15 mL) STERILE